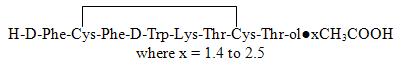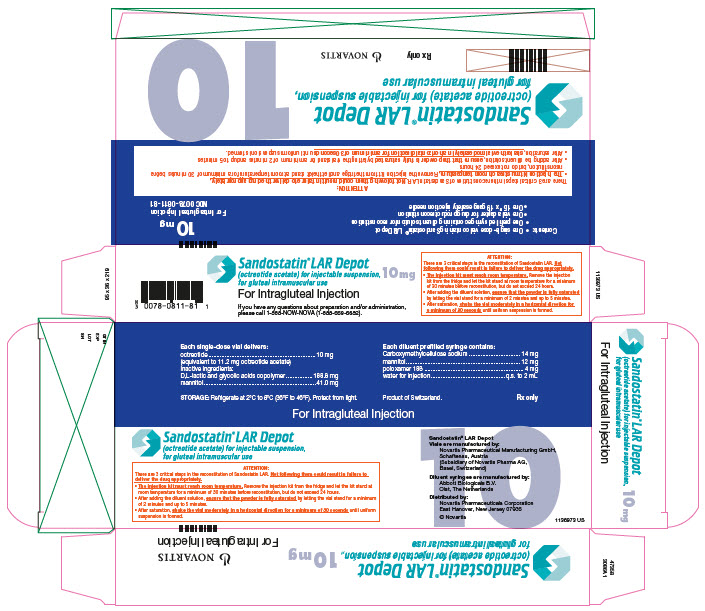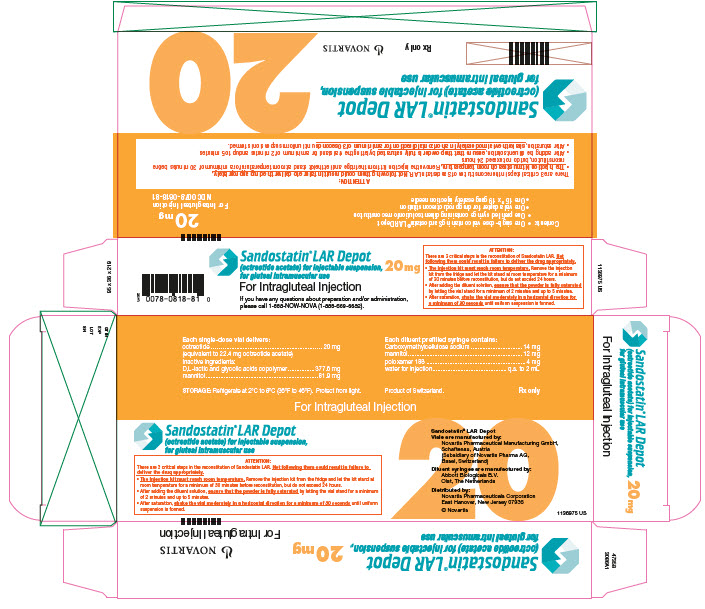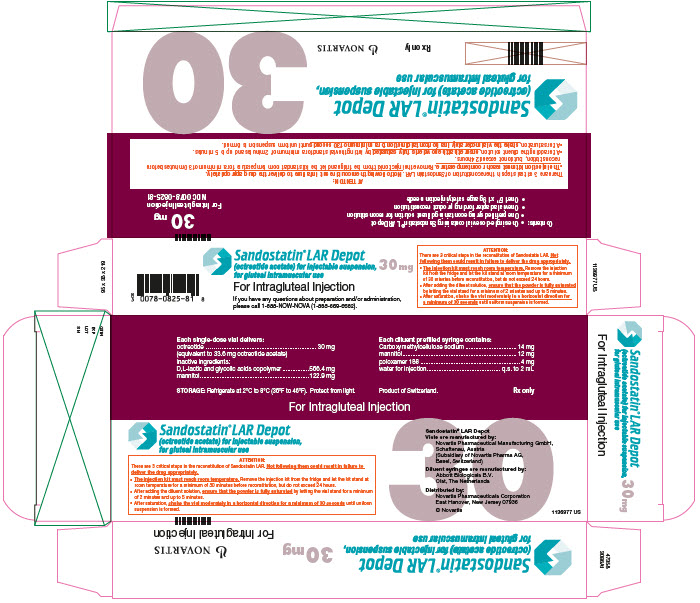 DRUG LABEL: Sandostatin LAR Depot
NDC: 0078-0811 | Form: KIT | Route: INTRAMUSCULAR
Manufacturer: Novartis Pharmaceuticals Corporation
Category: prescription | Type: HUMAN PRESCRIPTION DRUG LABEL
Date: 20251222

ACTIVE INGREDIENTS: OCTREOTIDE ACETATE 1.667 mg/1 mL
INACTIVE INGREDIENTS: LACTIC ACID, DL- 31.467 mg/1 mL; MANNITOL 6.833 mg/1 mL; CARBOXYMETHYLCELLULOSE SODIUM 7 mg/1 mL; MANNITOL 6 mg/1 mL; POLOXAMER 188 2 mg/1 mL; WATER 1 mL/1 mL

HIGHLIGHTS OF PRESCRIBING INFORMATION

These highlights do not include all the information needed to use SANDOSTATIN LAR DEPOT safely and effectively. See full prescribing information for SANDOSTATIN LAR DEPOT.
SANDOSTATIN® LAR DEPOT (octreotide acetate) for injectable suspension, for gluteal intramuscular use
Initial U.S. Approval: 1988

RECENT MAJOR CHANGES

Warnings and Precautions, Steatorrhea and Malabsorption of Dietary Fats (5.5) | 7/2024

1 INDICATIONS AND USAGE

SANDOSTATIN LAR DEPOT is a somatostatin analogue indicated for:

Treatment in patients who have responded to and tolerated Sandostatin Injection subcutaneous injection for:

- Acromegaly (1.1)
- Severe diarrhea/flushing episodes associated with metastatic carcinoid tumors (1.2)
- Profuse watery diarrhea associated with Vasoactive Intestinal Peptide (VIP) secreting tumors (1.3)

2 DOSAGE AND ADMINISTRATION

Patients Not Currently Receiving Sandostatin Injection Subcutaneously:

- Acromegaly: 50 mcg three times daily Sandostatin Injection subcutaneously for 2 weeks followed by SANDOSTATIN LAR DEPOT 20 mg intragluteally every 4 weeks for 3 months (2.1)
- Carcinoid Tumors and VIPomas: Sandostatin Injection subcutaneously 100 to 600 mcg/day in 2-4 divided doses for 2 weeks followed by SANDOSTATIN LAR DEPOT 20 mg every 4 weeks for 2 months (2.2)

Patients Currently Receiving Sandostatin Injection Subcutaneously:

- Acromegaly: 20 mg every 4 weeks for 3 months (2.1)
- Carcinoid Tumors and VIPomas: 20 mg every 4 weeks for 2 months (2.2)

Renal Impairment, Patients on Dialysis: 10 mg every 4 weeks (2.3)

Hepatic Impairment, Patients With Cirrhosis: 10 mg every 4 weeks (2.4)

3 DOSAGE FORMS AND STRENGTHS

For injectable suspension: strengths 10 mg per 6 mL, 20 mg per 6 mL, or 30 mg per 6 mL single-dose vials (3)

4 CONTRAINDICATIONS

None (4)

5 WARNINGS AND PRECAUTIONS

- Cholelithiasis and Complications of Cholelithiasis: Monitor periodically. Discontinue if complications of cholelithiasis are suspected (5.1)
- Glucose Metabolism: Hypoglycemia or hyperglycemia may occur. Glucose monitoring is recommended and anti-diabetic treatment may need adjustment (5.2)
- Thyroid Function: Hypothyroidism may occur. Monitor thyroid levels periodically (5.3)
- Cardiac Function: Bradycardia, arrhythmia, or conduction abnormalities may occur. Use with caution in at-risk patients (5.4)
- Steatorrhea and Malabsorption of Dietary Fats: New onset steatorrhea, stool discoloration, loose stools, abdominal bloating, and weight loss may occur. If new occurrence or worsening of these symptoms are reported, evaluate for potential pancreatic exocrine insufficiency (5.5)

6 ADVERSE REACTIONS

The most common adverse reactions, occurring in ≥ 20% of patients are:

- Acromegaly: diarrhea, cholelithiasis, abdominal pain, flatulence (6.1)
- Carcinoid Syndrome: back pain, fatigue, headache, abdominal pain, nausea, dizziness (6.1)

To report SUSPECTED ADVERSE REACTIONS, contact Novartis Pharmaceuticals Corporation at 1-888-669-6682 or FDA at 1-800-FDA-1088 or www.fda.gov/medwatch.

7 DRUG INTERACTIONS

- The following drugs require monitoring and possible dose adjustment when used with SANDOSTATIN LAR DEPOT: Cyclosporine, insulin, oral hypoglycemic agents, beta-blockers, and bromocriptine (7)
- Lutetium Lu 177 Dotatate Injection: Discontinue SANDOSTATIN LAR DEPOT at least 4 weeks prior to each lutetium Lu 177 dotatate dose (7.6)

8 USE IN SPECIFIC POPULATIONS

Females and Males of Reproductive Potential: Advise premenopausal females of the potential for an unintended pregnancy (8.3)

FULL PRESCRIBING INFORMATION

1 INDICATIONS AND USAGE

SANDOSTATIN LAR DEPOT 10 mg, 20 mg, and 30 mg is indicated in patients in whom initial treatment with Sandostatin Injection has been shown to be effective and tolerated.

1.1 Acromegaly

Long-term maintenance therapy in acromegalic patients who have had an inadequate response to surgery and/or radiotherapy, or for whom surgery and/or radiotherapy, is not an option. The goal of treatment in acromegaly is to reduce GH and IGF-1 levels to normal [see Clinical Studies (14), Dosage and Administration (2)].

1.2 Carcinoid Tumors

Long-term treatment of the severe diarrhea and flushing episodes associated with metastatic carcinoid tumors.

1.3 Vasoactive Intestinal Peptide Tumors (VIPomas)

Long-term treatment of the profuse watery diarrhea associated with VIP-secreting tumors.

1.4 Important Limitations of Use

In patients with carcinoid syndrome and VIPomas, the effect of Sandostatin Injection and SANDOSTATIN LAR DEPOT on tumor size, rate of growth and development of metastases, has not been determined.

2 DOSAGE AND ADMINISTRATION

- SANDOSTATIN LAR DEPOT should be administered by a trained healthcare provider. It is important to closely follow the mixing instructions included in the packaging. SANDOSTATIN LAR DEPOT must be administered immediately after mixing.
- Do not directly inject diluent without preparing suspension.
- The recommended needle size for administration of SANDOSTATIN LAR DEPOT is the 1½” 19 gauge safety injection needle (supplied in the drug product kit). For patients with a greater skin to muscle depth, a size 2” 19 gauge needle (not supplied) may be used.
- SANDOSTATIN LAR DEPOT should be administered intramuscularly (IM) in the gluteal region at 4-week intervals. Administration of SANDOSTATIN LAR DEPOT at intervals greater than 4 weeks is not recommended.
- Injection sites should be rotated in a systematic manner to avoid irritation. Deltoid injections should be avoided due to significant discomfort at the injection site when given in that area.
- SANDOSTATIN LAR DEPOT should never be administered intravenously or subcutaneously.

The following dosage regimens are recommended.

2.1 Acromegaly

Patients Not Currently Receiving Octreotide Acetate

Patients not currently receiving octreotide acetate should begin therapy with Sandostatin Injection given subcutaneously in an initial dose of 50 mcg three times daily which may be titrated. Most patients require doses of 100 mcg to 200 mcg three times daily for maximum effect but some patients require up to 500 mcg three times daily.

Patients should be maintained on Sandostatin Injection subcutaneous for at least 2 weeks to determine tolerance to octreotide acetate. Patients who are considered to be “responders” to the drug, based on GH and IGF-1 levels and who tolerate the drug, can then be switched to SANDOSTATIN LAR DEPOT in the dosage scheme described below (Patients Currently Receiving Sandostatin Injection).

Patients Currently Receiving Sandostatin Injection

Patients currently receiving Sandostatin Injection can be switched directly to SANDOSTATIN LAR DEPOT in a dose of 20 mg given IM intragluteally at 4-week intervals for 3 months. After 3 months, dosage may be adjusted as follows:

- GH ≤ 2.5 ng/mL, IGF-1 normal, and clinical symptoms controlled: maintain SANDOSTATIN LAR DEPOT dosage at 20 mg every 4 weeks
- GH > 2.5 ng/mL, IGF-1 elevated, and/or clinical symptoms uncontrolled, increase SANDOSTATIN LAR DEPOT dosage to 30 mg every 4 weeks
- GH ≤ 1 ng/mL, IGF-1 normal, and clinical symptoms controlled, reduce SANDOSTATIN LAR DEPOT dosage to 10 mg every 4 weeks
- If GH, IGF-1, or symptoms are not adequately controlled at a dose of 30 mg, the dose may be increased to 40 mg every 4 weeks. Doses higher than 40 mg are not recommended.

In patients who have received pituitary irradiation, SANDOSTATIN LAR DEPOT should be withdrawn yearly for approximately 8 weeks to assess disease activity. If GH or IGF-1 levels increase and signs and symptoms recur, SANDOSTATIN LAR DEPOT therapy may be resumed.

2.2 Carcinoid Tumors and VIPomas

Patients Not Currently Receiving Octreotide Acetate

Patients not currently receiving octreotide acetate should begin therapy with Sandostatin Injection given subcutaneously. The suggested daily dosage for carcinoid tumors during the first 2 weeks of therapy ranges from 100 to 600 mcg/day in 2 to 4 divided doses (mean daily dosage is 300 mcg). Some patients may require doses up to 1,500 mcg/day. The suggested daily dosage for VIPomas is 200 to 300 mcg in 2 to 4 divided doses (range, 150 to 750 mcg); dosage may be adjusted on an individual basis to control symptoms but usually doses above 450 mcg/day are not required.

Sandostatin Injection should be continued for at least 2 weeks. Thereafter, patients who are considered “responders” to octreotide acetate, and who tolerate the drug, may be switched to SANDOSTATIN LAR DEPOT in the dosage regimen as described below (Patients Currently Receiving Sandostatin Injection).

Patients Currently Receiving Sandostatin Injection

Patients currently receiving Sandostatin Injection can be switched to SANDOSTATIN LAR DEPOT in a dosage of 20 mg given IM intragluteally at 4-week intervals for 2 months. Because of the need for serum octreotide to reach therapeutically effective levels following initial injection of SANDOSTATIN LAR DEPOT, carcinoid tumor and VIPoma patients should continue to receive Sandostatin Injection subcutaneously for at least 2 weeks in the same dosage they were taking before the switch. Failure to continue subcutaneous injections for this period may result in exacerbation of symptoms (some patients may require 3 or 4 weeks of such therapy).

After 2 months, dosage may be adjusted as follows:

- If symptoms are adequately controlled, consider a dose reduction to 10 mg for a trial period. If symptoms recur, dosage should then be increased to 20 mg every 4 weeks. Many patients can, however, be satisfactorily maintained at a 10-mg dose every 4 weeks.
- If symptoms are not adequately controlled, increase SANDOSTATIN LAR DEPOT to 30 mg every 4 weeks. Patients who achieve good control on a 20-mg dose may have their dose lowered to 10 mg for a trial period. If symptoms recur, dosage should then be increased to 20 mg every 4 weeks.
- Dosages higher than 30 mg are not recommended.

Despite good overall control of symptoms, patients with carcinoid tumors and VIPomas often experience periodic exacerbation of symptoms (regardless of whether they are being maintained on Sandostatin Injection or SANDOSTATIN LAR DEPOT). During these periods, they may be given Sandostatin Injection subcutaneously for a few days at the dosage they were receiving prior to switching to SANDOSTATIN LAR DEPOT. When symptoms are again controlled, the Sandostatin Injection subcutaneous can be discontinued.

2.3 Special Populations: Renal Impairment

In patients with renal failure requiring dialysis, the starting dose should be 10 mg every 4 weeks. In other patients with renal impairment, the starting dose should be similar to a nonrenal patient (i.e., 20 mg every 4 weeks) [see Clinical Pharmacology (12)].

2.4 Special Populations: Hepatic Impairment – Cirrhotic Patients

In patients with established cirrhosis of the liver, the starting dose should be 10 mg every 4 weeks [see Clinical Pharmacology (12.3)].

3 DOSAGE FORMS AND STRENGTHS

SANDOSTATIN LAR DEPOT is available in single-dose kits for injectable suspension containing a 6-mL single-dose vial of 10 mg, 20 mg, or 30 mg strength, a prefilled syringe containing 2 mL of diluent, one vial adapter, and one sterile 1½” 19 gauge safety injection needle. An instruction booklet for the preparation of drug suspension for injection is also included with each kit.

4 CONTRAINDICATIONS

None.

5 WARNINGS AND PRECAUTIONS

5.1 Cholelithiasis and Complications of Cholelithiasis

SANDOSTATIN LAR DEPOT may inhibit gallbladder contractility and decrease bile secretion, which may lead to gallbladder abnormalities or sludge. There have been postmarketing reports of cholelithiasis (gallstones) resulting in complications, including cholecystitis, cholangitis, pancreatitis and requiring cholecystectomy in patients taking SANDOSTATIN LAR DEPOT [see Adverse Reactions (6)]. Patients should be monitored periodically. If complications of cholelithiasis are suspected, discontinue SANDOSTATIN LAR DEPOT and treat appropriately.

5.2 Hyperglycemia and Hypoglycemia

Octreotide alters the balance between the counter-regulatory hormones, insulin, glucagon, and growth hormone (GH), which may result in hypoglycemia or hyperglycemia. Blood glucose levels should be monitored when SANDOSTATIN LAR DEPOT treatment is initiated, or when the dose is altered. Anti-diabetic treatment should be adjusted accordingly [see Adverse Reactions (6)].

5.3 Thyroid Function Abnormalities

Octreotide suppresses the secretion of thyroid-stimulating hormone (TSH), which may result in hypothyroidism. Baseline and periodic assessment of thyroid function (TSH, total and/or free T4) is recommended during chronic octreotide therapy [see Adverse Reactions (6)].

5.4 Cardiac Function Abnormalities

In both acromegalic and carcinoid syndrome patients, bradycardia, arrhythmias and conduction abnormalities have been reported during octreotide therapy. Other electrocardiogram (ECG) changes were observed, such as QT prolongation, axis shifts, early repolarization, low voltage, R/S transition, early R wave progression, and nonspecific ST-T wave changes. The relationship of these events to octreotide acetate is not established because many of these patients have underlying cardiac disease. Dose adjustments in drugs, such as beta-blockers that have bradycardic effects may be necessary. In one acromegalic patient with severe congestive heart failure (CHF), initiation of Sandostatin Injection-therapy resulted in worsening of CHF with improvement when drug was discontinued. Confirmation of a drug effect was obtained with a positive rechallenge [see Adverse Reactions (6)].

5.5 Steatorrhea and Malabsorption of Dietary Fats

New onset steatorrhea, stool discoloration and loose stool have been reported in patients receiving somatostatin analogs, including SANDOSTATIN LAR DEPOT. Somatostatin analogs reversibly inhibit secretion of pancreatic enzymes and bile acids, which may result in malabsorption of dietary fats and subsequent symptoms of steatorrhea, loose stools, abdominal bloating, and weight loss. If new occurrence or worsening of these symptoms are reported in patients receiving SANDOSTATIN LAR DEPOT, evaluate patients for potential pancreatic exocrine insufficiency and manage accordingly.

5.6 Changes in Vitamin B12 Levels

Depressed vitamin B12 levels and abnormal Schilling tests have been observed in some patients receiving octreotide therapy, and monitoring of vitamin B12 levels is recommended during therapy with SANDOSTATIN LAR DEPOT.

5.7 Changes in Zinc Levels

Octreotide has been investigated for the reduction of excessive fluid loss from the GI tract in patients with conditions producing such a loss. If such patients are receiving total parenteral nutrition (TPN), serum zinc may rise excessively when the fluid loss is reversed. Patients on TPN and octreotide should have periodic monitoring of zinc levels.

5.8 Monitoring: Laboratory Tests

Laboratory tests that may be helpful as biochemical markers in determining and following patient response depend on the specific tumor. Based on diagnosis, measurement of the following substances may be useful in monitoring the progress of therapy [see Dosage and Administration (2.1, 2.2)].

Acromegaly: Growth Hormone, IGF-1 (somatomedin C)

Carcinoid: 5-HIAA (urinary 5-hydroxyindole acetic acid), plasma serotonin, plasma Substance P

VIPoma: VIP (plasma vasoactive intestinal peptide) baseline and periodic total and/or free T4 measurements should be performed during chronic therapy

5.9 Drug Interactions

Octreotide has been associated with alterations in nutrient absorption, so it may have an effect on absorption of orally administered drugs. Concomitant administration of octreotide injection with cyclosporine may decrease blood levels of cyclosporine [see Drug Interactions (7.1)].

6 ADVERSE REACTIONS

The following clinically significant adverse reactions are described elsewhere in the labeling:

- Cholelithiasis and Complications of Cholelithiasis [see Warnings and Precautions (5.1)]
- Hyperglycemia and Hypoglycemia [see Warnings and Precautions (5.2)]
- Thyroid Function Abnormalities [see Warnings and Precautions (5.3)]
- Cardiac Function Abnormalities [see Warnings and Precautions (5.4)]
- Steatorrhea and Malabsorption of Dietary Fats [see Warnings and Precautions (5.5)]
- Changes in Vitamin B12 Levels [see Warnings and Precautions (5.6)]
- Changes in Zinc Levels [see Warnings and Precautions (5.7)]
- Monitoring: Laboratory Tests [see Warnings and Precautions (5.8)]
- Drug Interactions [see Warnings and Precautions (5.9)]

6.1 Clinical Trials Experience

Because clinical trials are conducted under widely varying conditions, adverse reaction rates observed in the clinical trials of a drug cannot be directly compared to rates in the clinical trial of another drug and may not reflect the rates observed in practice.

Acromegaly

The safety of SANDOSTATIN LAR DEPOT in the treatment of acromegaly has been evaluated in three Phase 3 studies in 261 patients, including 209 exposed for 48 weeks and 96 exposed for greater than 108 weeks. SANDOSTATIN LAR DEPOT was studied primarily in a double-blind, cross-over manner. Patients on subcutaneous Sandostatin Injection were switched to the LAR formulation followed by an open-label extension. The population age range was 14 to 81 years old and 53% were female. Approximately 35% of these acromegaly patients had not been treated with surgery and/or radiation. Most patients received a starting dose of 20 mg every 4 weeks intramuscularly. Dose was up or down titrated based on efficacy and tolerability to a final dose between 10 mg to 60 mg every 4 weeks. Table 1 below reflects adverse events from these studies regardless of presumed causality to study drug.

Table 1. Adverse Events Occurring in ≥ 10% of Acromegalic Patients in the Phase 3 Studies
WHO Preferred Term | Phase 3 Studies (Pooled) Number (%) of Subjects with AEs 10 mg/20 mg/30 mg (n = 261) n (%)
Diarrhea | 93 (35.6)
Abdominal Pain | 75 (28.7)
Flatulence | 66 (25.3)
Influenza-Like Symptoms | 52 (19.9)
Constipation | 46 (17.6)
Headache | 40 (15.3)
Anemia | 40 (15.3)
Injection-Site Pain | 36 (13.8)
Cholelithiasis | 35 (13.4)
Hypertension | 33 (12.6)
Dizziness | 30 (11.5)
Fatigue | 29 (11.1)
Abbreviation: AEs, adverse events.

The safety of SANDOSTATIN LAR DEPOT in the treatment of acromegaly was also evaluated in a postmarketing randomized Phase 4 study. One-hundred four (104) patients were randomized to either pituitary surgery or 20 mg of SANDOSTATIN LAR DEPOT. All the patients were treatment naïve (‘de novo’). Crossover was allowed according to treatment response and a total of 76 patients were exposed to Sandostatin LAR. Approximately half of the patients initially randomized to SANDOSTATIN LAR DEPOT were exposed to SANDOSTATIN LAR DEPOT up to 1 year. The population age range was between 20 to 76 years old, 45% were female, 93% were Caucasian, and 1% Black. The majority of these patients were exposed to 30 mg every 4 weeks. Table 2 below reflects the adverse events occurring in this study regardless of presumed causality to study drug.

Table 2. Adverse Events Occurring in ≥ 10% of Acromegalic Patients in Phase 4 Study
WHO Preferred Term | Phase 4 Study SANDOSTATIN LAR DEPOT N = 76 n (%) | Phase 4 Study Surgery N = 64 n (%)
Diarrhea | 36 (47.4) | 2 (3.1)
Cholelithiasis | 29 (38.2) | 3 (4.7)
Abdominal Pain | 19 (25.0) | 2 (3.1)
Nausea | 12 (15.8) | 5 (7.8)
Alopecia | 10 (13.2) | 5 (7.8)
Injection-Site Pain | 9 (11.8) | 0
Abdominal Pain Upper | 8 (10.5) | 0
Headache | 8 (10.5) | 6 (9.4)
Epistaxis | 0 | 7 (10.9)

Gallbladder Abnormalities

Single doses of Sandostatin Injection have been shown to inhibit gallbladder contractility and decrease bile secretion in normal volunteers. In clinical trials with Sandostatin Injection (primarily patients with acromegaly or psoriasis) in patients who had not previously received octreotide acetate, the incidence of biliary tract abnormalities was 63% (27% gallstones, 24% sludge without stones, 12% biliary duct dilatation). The incidence of stones or sludge in patients who received Sandostatin Injection for 12 months or longer was 52%. The incidence of gallbladder abnormalities did not appear to be related to age, sex, or dose but was related to duration of exposure.

In clinical trials, 52% of acromegalic patients, most of whom received SANDOSTATIN LAR DEPOT for 12 months or longer, developed new biliary abnormalities including gallstones, microlithiasis, sediment, sludge, and dilatation. The incidence of new cholelithiasis was 22%, of which 7% were microstones.

Across all trials, a few patients developed acute cholecystitis, ascending cholangitis, biliary obstruction, cholestatic hepatitis, or pancreatitis during octreotide therapy or following its withdrawal. One patient developed ascending cholangitis during Sandostatin Injection therapy and died. Despite the high incidence of new gallstones in patients receiving octreotide acetate, 1% of patients developed acute symptoms requiring cholecystectomy.

Glucose Metabolism - Hypoglycemia/Hyperglycemia

In acromegaly patients treated with either Sandostatin Injection or SANDOSTATIN LAR DEPOT, hypoglycemia occurred in approximately 2% and hyperglycemia in approximately 15% of patients [see Warnings and Precautions (5.2)].

Hypothyroidism

In acromegaly patients receiving Sandostatin Injection, 12% developed biochemical hypothyroidism, 8% developed goiter, and 4% required initiation of thyroid replacement therapy while receiving Sandostatin Injection. In acromegalic patients treated with SANDOSTATIN LAR DEPOT, hypothyroidism was reported as an adverse event in 2% and goiter in 2%. Two patients receiving SANDOSTATIN LAR DEPOT required initiation of thyroid hormone replacement therapy [see Warnings and Precautions (5.3)].

Cardiac

In acromegalic patients, sinus bradycardia (< 50 bpm) developed in 25%; conduction abnormalities occurred in 10% and arrhythmias developed in 9% of patients during Sandostatin Injection-therapy. The relationship of these events to octreotide acetate is not established because many of these patients have underlying cardiac disease [see Warnings and Precautions (5.4)].

Gastrointestinal

The most common symptoms are gastrointestinal. The overall incidence of the most frequent of these symptoms in clinical trials of acromegalic patients treated for approximately 1 to 4 years is shown in Table 3.

Table 3. Number (%) of Acromegalic Patients With Common GI Adverse Events
Adverse Event | Sandostatin Injection S.C. Three Times Daily n = 114 |  | SANDOSTATIN LAR DEPOT Every 28 Days n = 261
 | n | % | n | %
Diarrhea | 66 | (57.9) | 95 | (36.4)
Abdominal Pain or Discomfort | 50 | (43.9) | 76 | (29.1)
Nausea | 34 | (29.8) | 27 | (10.3)
Flatulence | 15 | (13.2) | 67 | (25.7)
Constipation | 10 | (8.8) | 49 | (18.8)
Vomiting | 5 | (4.4) | 17 | (6.5)

Only 2.6% of the patients on Sandostatin Injection in US clinical trials discontinued therapy due to these symptoms. No acromegalic patient receiving SANDOSTATIN LAR DEPOT discontinued therapy for a GI event.

In patients receiving SANDOSTATIN LAR DEPOT, the incidence of diarrhea was dose related. Diarrhea, abdominal pain, and nausea developed primarily during the first month of treatment with SANDOSTATIN LAR DEPOT. Thereafter, new cases of these events were uncommon. The vast majority of these events were mild-to-moderate in severity.

In rare instances, gastrointestinal adverse effects may resemble acute intestinal obstruction, with progressive abdominal distention, severe epigastric pain, abdominal tenderness, and guarding.

Dyspepsia, steatorrhea, discoloration of feces, and tenesmus were reported in 4% to 6% of patients.

In a clinical trial of carcinoid syndrome, nausea, abdominal pain, and flatulence were reported in 27% to 38% and constipation or vomiting in 15% to 21% of patients treated with SANDOSTATIN LAR DEPOT. Diarrhea was reported as an adverse event in 14% of patients, but since most of the patients had diarrhea as a symptom of carcinoid syndrome, it is difficult to assess the actual incidence of drug-related diarrhea.

Pain at the Injection Site

Pain on injection, which is generally mild-to-moderate, and short-lived (usually about 1 hour) is dose related, being reported by 2%, 9%, and 11% of acromegalic patients receiving doses of 10 mg, 20 mg, and 30 mg, respectively, of SANDOSTATIN LAR DEPOT. In carcinoid patients, where a diary was kept, pain at the injection site was reported by about 20%-25% at a 10-mg dose and about 30%-50% at the 20-mg and 30-mg dose.

Antibodies to Octreotide

Studies to date have shown that antibodies to octreotide develop in up to 25% of patients treated with octreotide acetate. These antibodies do not influence the degree of efficacy response to octreotide; however, in two acromegalic patients who received Sandostatin Injection, the duration of GH suppression following each injection was about twice as long as in patients without antibodies. It has not been determined whether octreotide antibodies will also prolong the duration of GH suppression in patients being treated with SANDOSTATIN LAR DEPOT.

Carcinoid and VIPomas

The safety of SANDOSTATIN LAR DEPOT in the treatment of carcinoid tumors and VIPomas has been evaluated in one Phase 3 study. Study 1 randomized 93 patients with carcinoid syndrome to SANDOSTATIN LAR DEPOT 10 mg, 20 mg, or 30 mg in a blind fashion or to open-label Sandostatin Injection subcutaneously. The population age range was between 25 to 78 years old and 44% were female, 95% were Caucasian and 3% Black. All the patients had symptom control on their previous Sandostatin subcutaneous treatment. Eighty (80) patients finished the initial 24 weeks of Sandostatin exposure in Study 1. In Study 1, comparable numbers of patients were randomized to each dose. Table 4 below reflects the adverse events occurring in ≥ 15% of patients regardless of presumed causality to study drug.

Table 4. Adverse Events Occurring in ≥ 15% of Carcinoid Tumor and VIPoma Patients in Study 1
 | Number (%) of Subjects With AEs (n = 93)
WHO Preferred Term | S.C. N = 26 | 10 mg N = 22 | 20 mg N = 20 | 30 mg N = 25
Abdominal Pain | 8 (30.8) | 8 (35.4) | 2 (10.0) | 5 (20.0)
Arthropathy | 5 (19.2) | 2 (9.1) | 3 (15.0) | 2 (8.0)
Back Pain | 7 (26.9) | 6 (27.3) | 2 (10.0) | 2 (8.0)
Dizziness | 4 (15.4) | 4 (18.2) | 4 (20.0) | 5 (20.0)
Fatigue | 3 (11.5) | 7 (31.8) | 2 (10.0) | 2 (8.0)
Flatulence | 3 (11.5) | 2 (9.1) | 2 (10.0) | 4 (16.0)
Generalized Pain | 4 (15.4) | 2 (9.1) | 3 (15.0) | 1 (4.0)
Headache | 5 (19.2) | 4 (18.2) | 6 (30.0) | 4 (16.0)
Musculoskeletal Pain | 4 (15.4) | 0 | 1 (5.0) | 0
Myalgia | 0 | 4 (18.2) | 1 (5.0) | 1 (4.0)
Nausea | 8 (30.8) | 9 (40.9) | 6 (30.0) | 6 (24.0)
Pruritus | 0 | 4 (18.2) | 0 | 0
Rash | 1 (3.8) | 0 | 3 (15.0) | 0
Sinusitis | 4 (15.4) | 0 | 1 (5.0) | 3 (12.0)
URTI | 6 (23.1) | 4 (18.2) | 2 (10.0) | 3 (12.0)
Vomiting | 3 (11.5) | 0 | 0 | 4 (16.0)

Gallbladder Abnormalities

In clinical trials, 62% of malignant carcinoid patients, who received SANDOSTATIN LAR DEPOT for up to 18 months, developed new biliary abnormalities including jaundice, gallstones, sludge, and dilatation. New gallstones occurred in a total of 24% of patients.

Glucose Metabolism - Hypoglycemia/Hyperglycemia

In carcinoid patients, hypoglycemia occurred in 4% and hyperglycemia in 27% of patients treated with SANDOSTATIN LAR DEPOT [see Warnings and Precautions (5.2)].

Hypothyroidism

In carcinoid patients, hypothyroidism has only been reported in isolated patients and goiter has not been reported [see Warnings and Precautions (5.3)].

Cardiac

Electrocardiograms were performed only in carcinoid patients receiving SANDOSTATIN LAR DEPOT. In carcinoid syndrome patients, sinus bradycardia developed in 19%, conduction abnormalities occurred in 9%, and arrhythmias developed in 3%. The relationship of these events to octreotide acetate is not established because many of these patients have underlying cardiac disease [see Warnings and Precautions (5.4)].

Other Clinical Studies Adverse Events

Other clinically significant adverse events (relationship to drug not established) in acromegalic and/or carcinoid syndrome patients receiving SANDOSTATIN LAR DEPOT were malignant hyperpyrexia, cerebral vascular disorder, rectal bleeding, ascites, pulmonary embolism, pneumonia, and pleural effusion.

6.2 Postmarketing Experience

The following adverse reactions have been identified during the postapproval use of SANDOSTATIN LAR DEPOT. Because these reactions are reported voluntarily from a population of uncertain size, it is not always possible to reliably estimate their frequency or establish a causal relationship to drug exposure.

Blood and lymphatic: pancytopenia, thrombocytopenia

Cardiac: myocardial infarction, cardiac arrest, atrial fibrillation

Ear and labyrinth: deafness

Endocrine: diabetes insipidus, adrenal insufficiency in patients 18 months of age and under, pituitary apoplexy

Eye: glaucoma, visual field defect, scotoma, retinal vein thrombosis

Gastrointestinal: intestinal obstruction, peptic/gastric ulcer, abdomen enlarged, pancreatic exocrine insufficiency

General and administration site: generalized edema, facial edema

Hepatobiliary: gallbladder polyp, fatty liver, hepatitis

Immune: anaphylactoid reactions including anaphylactic shock

Infections and infestations: appendicitis

Laboratory abnormalities: increased liver enzymes, CK increased, creatinine increased

Metabolism and nutrition: diabetes mellitus

Musculoskeletal: arthritis, joint effusion, Raynaud’s syndrome

Nervous system: convulsions, aneurysm, intracranial hemorrhage, hemiparesis, paresis, suicide attempt, paranoia, migraines, Bell’s palsy, aphasia

Renal and urinary: renal failure, renal insufficiency

Reproductive and breast: gynecomastia, galactorrhea, libido decrease, breast carcinoma

Respiratory: status asthmaticus, pulmonary hypertension, pulmonary nodule, pneumothorax aggravated

Skin and subcutaneous tissue: urticaria, cellulitis, petechiae

Vascular: orthostatic hypotension, hematuria, gastrointestinal hemorrhage, arterial thrombosis of the arm

7 DRUG INTERACTIONS

7.1 Cyclosporine

Concomitant administration of octreotide injection with cyclosporine may decrease blood levels of cyclosporine and result in transplant rejection.

7.2 Insulin and Oral Hypoglycemic Drugs

Octreotide inhibits the secretion of insulin and glucagon. Therefore, blood glucose levels should be monitored when SANDOSTATIN LAR DEPOT treatment is initiated and when the dose is altered and anti-diabetic treatment should be adjusted accordingly.

7.3 Bromocriptine

Concomitant administration of octreotide and bromocriptine increases the availability of bromocriptine.

7.4 Other Concomitant Drug Therapy

Concomitant administration of bradycardia-inducing drugs (e.g., beta-blockers) may have an additive effect on the reduction of heart rate associated with octreotide. Dose adjustments of concomitant medication may be necessary.

Octreotide has been associated with alterations in nutrient absorption, so it may have an effect on absorption of orally administered drugs.

7.5 Drug Metabolism Interactions

Limited published data indicate that somatostatin analogs may decrease the metabolic clearance of compounds known to be metabolized by cytochrome P450 enzymes, which may be due to the suppression of growth hormone. Since it cannot be excluded that octreotide may have this effect, other drugs mainly metabolized by CYP3A4 and which have a low therapeutic index (e.g., quinidine, terfenadine) should therefore be used with caution.

7.6 Lutetium Lu 177 Dotatate Injection

Octreotide competitively binds to somatostatin receptors and may interfere with the efficacy of lutetium Lu 177 dotatate. Discontinue SANDOSTATIN LAR DEPOT at least 4 weeks prior to each lutetium Lu 177 dotatate dose.

8 USE IN SPECIFIC POPULATIONS

8.1 Pregnancy

Risk Summary

The limited data with SANDOSTATIN LAR DEPOT in pregnant women are insufficient to inform a drug-associated risk for major birth defects and miscarriage. In animal reproduction studies, no adverse developmental effects were observed with intravenous administration of octreotide to pregnant rats and rabbits during organogenesis at doses 7- and 13-times, respectively the maximum recommended human dose (MRHD) of 1.5 mg/day based on body surface area (BSA). Transient growth retardation, with no impact on postnatal development, was observed in rat offspring from a pre- and post-natal study of octreotide at intravenous doses below the MRHD based on BSA (see Data).

The estimated background risk of major birth defects and miscarriage for the indicated population is unknown. In the U.S. general population, the estimated background risk of major birth defects and miscarriage in clinically recognized pregnancies is 2% to 4% and 15% to 20%, respectively.

Data

Animal Data

In embryo-fetal development studies in rats and rabbits, pregnant animals received intravenous doses of octreotide up to 1 mg/kg/day during the period of organogenesis. A slight reduction in body weight gain was noted in pregnant rats at 0.1 and 1 mg/kg/day. There were no maternal effects in rabbits or embryo-fetal effects in either species up to the maximum dose tested. At 1 mg/kg/day in rats and rabbits, the dose multiple was approximately 7- and 13-times, respectively, at the highest recommended human dose of 1.5 mg/day based on BSA.

In a pre- and post-natal development rat study at intravenous doses of 0.02-1 mg/kg/day, a transient growth retardation of the offspring was observed at all doses which was possibly a consequence of growth hormone inhibition by octreotide. The doses attributed to the delayed growth are below the human dose of 1.5 mg/day, based on BSA.

8.2 Lactation

Risk Summary

There is no information available on the presence of SANDOSTATIN LAR DEPOT in human milk, the effects of the drug on the breastfed infant, or the effects of the drug on milk production. Studies show that octreotide administered subcutaneously passes into the milk of lactating rats; however, due to species-specific differences in lactation physiology, animal data may not reliably predict drug levels in human milk (see Data). The developmental and health benefits of breastfeeding should be considered along with the mother’s clinical need for SANDOSTATIN LAR DEPOT, and any potential adverse effects on the breastfed child from SANDOSTATIN LAR DEPOT or from the underlying maternal condition.

Data

Following a subcutaneous dose (1 mg/kg) of octreotide to lactating rats, transfer of octreotide into milk was observed at a low concentration compared to plasma (milk/plasma ratio of 0.009).

8.3 Females and Males of Reproductive Potential

Discuss the potential for unintended pregnancy with premenopausal women as the therapeutic benefits of a reduction in GH levels and normalization of insulin-like growth factor 1 (IGF-1) concentration in acromegalic females treated with octreotide may lead to improved fertility.

8.4 Pediatric Use

Safety and efficacy of SANDOSTATIN LAR DEPOT in the pediatric population have not been demonstrated.

No formal controlled clinical trials have been performed to evaluate the safety and effectiveness of SANDOSTATIN LAR DEPOT in pediatric patients under 6 years of age. In postmarketing reports, serious adverse events, including hypoxia, necrotizing enterocolitis, and death, have been reported with Sandostatin use in children, most notably in children under 2 years of age. The relationship of these events to octreotide acetate has not been established as the majority of these pediatric patients had serious underlying comorbid conditions.

The efficacy and safety of SANDOSTATIN LAR DEPOT was examined in a single randomized, double-blind, placebo-controlled, 6-month pharmacokinetics study in 60 pediatric patients age 6 to 17 years with hypothalamic obesity resulting from cranial insult. The mean octreotide concentration after 6 doses of 40 mg SANDOSTATIN LAR DEPOT administered by IM injection every four weeks was approximately 3 ng/mL. Steady-state concentrations were achieved after 3 injections of a 40-mg dose. Mean BMI increased 0.1 kg/m^2 in SANDOSTATIN LAR DEPOT-treated subjects compared to 0.0 kg/m^2 in saline control-treated subjects. Efficacy was not demonstrated. Diarrhea occurred in 11 of 30 (37%) patients treated with SANDOSTATIN LAR DEPOT. No unexpected adverse events were observed. However, with SANDOSTATIN LAR DEPOT 40 mg once a month, the incidence of new cholelithiasis in this pediatric population (33%) was higher than that seen in other adult indications, such as acromegaly (22%) or malignant carcinoid syndrome (24%), where SANDOSTATIN LAR DEPOT was dosed at 10 mg to 30 mg once a month.

8.5 Geriatric Use

Clinical studies of Sandostatin did not include sufficient numbers of subjects age 65 years and over to determine whether they respond differently from younger subjects. Other reported clinical experience has not identified differences in responses between the elderly and younger patients. In general, dose selection for an elderly patient should be cautious, usually starting at the low end of the dosing range, reflecting the greater frequency of decreased hepatic, renal, or cardiac function, and of concomitant disease or other drug therapy.

8.6 Renal Impairment

In patients with renal failure requiring dialysis, the starting dose should be 10 mg. This dose should be up titrated based on clinical response and speed of response as deemed necessary by the physician. In patients with mild, moderate, or severe renal impairment there is no need to adjust the starting dose of Sandostatin. The maintenance dose should be adjusted thereafter based on clinical response and tolerability as in nonrenal patients [see Clinical Pharmacology (12)].

8.7 Hepatic Impairment-Cirrhotic Patients

In patients with established liver cirrhosis, the starting dose should be 10 mg. This dose should be up titrated based on clinical response and speed of response as deemed necessary by the physician. Once at a higher dose, patient should be maintained or dose adjusted based on response and tolerability as in any noncirrhotic patients [see Clinical Pharmacology (12)].

10 OVERDOSAGE

Doses of 2.5 mg (2500 mcg) of Sandostatin Injection subcutaneously have caused hypoglycemia, flushing, dizziness, and nausea.

Contact Poison Control (1-800-222-1222) for latest recommendations.

11 DESCRIPTION

Octreotide is the acetate salt of a cyclic octapeptide. It is a long-acting octapeptide with pharmacologic properties mimicking those of the natural hormone somatostatin. Octreotide is known chemically as L-Cysteinamide, D-phenylalanyl-L-cysteinyl-L-phenylalanyl-D-tryptophyl-L-lysyl-L-threonyl-N-[2-hydroxy-1-(hydroxy-methyl) propyl]-, cyclic (2→7)-disulfide; [R-(R*,R*)].

The molecular weight of octreotide is 1019.3 g/mol (free peptide, C49H66N10O10S2) and its amino acid sequence is:

SANDOSTATIN LAR DEPOT is available in a single-dose vial containing the sterile drug product, which when mixed with diluent, becomes a suspension that is given as a monthly intragluteal injection. The octreotide is uniformly distributed within the microspheres which are made of a biodegradable glucose star polymer, D,L-lactic and glycolic acids copolymer. Sterile mannitol is added to the microspheres to improve suspendability.

SANDOSTATIN LAR DEPOT is available as: sterile 6-mL single-dose vials in 3 strengths delivering 10 mg, 20 mg, or 30 mg octreotide-free peptide. Each single-dose vial of SANDOSTATIN LAR DEPOT delivers:

Name of Ingredient | 10 mg | 20 mg | 30 mg
octreotide acetate | 11.2 mg* | 22.4 mg* | 33.6 mg*
D,L-lactic and glycolic acids copolymer | 188.8 mg | 377.6 mg | 566.4 mg
mannitol | 41.0 mg | 81.9 mg | 122.9 mg
*Equivalent to 10 mg, 20 mg, or 30 mg octreotide, respectively.

Each prefilled syringe of diluent contains:
carboxymethylcellulose sodium | 14 mg
mannitol | 12 mg
poloxamer 188 | 4 mg
water for injection | q.s. to 2 mL

12 CLINICAL PHARMACOLOGY

SANDOSTATIN LAR DEPOT is a long-acting dosage form consisting of microspheres of the biodegradable glucose star polymer, D,L-lactic and glycolic acids copolymer, containing octreotide acetate. It maintains all of the clinical and pharmacological characteristics of the immediate-release dosage form Sandostatin Injection with the added feature of slow release of octreotide acetate from the site of injection, reducing the need for frequent administration. This slow release occurs as the polymer biodegrades, primarily through hydrolysis. SANDOSTATIN LAR DEPOT is designed to be injected intramuscularly (intragluteally) once every 4 weeks.

12.1 Mechanism of Action

Octreotide exerts pharmacologic actions similar to the natural hormone, somatostatin. It is an even more potent inhibitor of growth hormone, glucagon, and insulin than somatostatin. Like somatostatin, it also suppresses LH response to GnRH, decreases splanchnic blood flow, and inhibits release of serotonin, gastrin, vasoactive intestinal peptide, secretin, motilin, and pancreatic polypeptide.

By virtue of these pharmacological actions, octreotide has been used to treat the symptoms associated with metastatic carcinoid tumors (flushing and diarrhea), and VIP secreting adenomas (watery diarrhea).

12.2 Pharmacodynamics

Octreotide substantially reduces and in many cases can normalize growth hormone and/or IGF-1 (somatomedin C) levels in patients with acromegaly.

Single doses of Sandostatin Injection given subcutaneously have been shown to inhibit gallbladder contractility and to decrease bile secretion in normal volunteers. In controlled clinical trials, the incidence of gallstone or biliary sludge formation was markedly increased [see Warnings and Precautions (5.1)].

Octreotide may cause clinically significant suppression of TSH.

12.3 Pharmacokinetics

Sandostatin Injection

According to data obtained with the immediate-release formulation, Sandostatin Injection solution, after subcutaneous injection, octreotide is absorbed rapidly and completely from the injection site. Peak concentrations of 5.2 ng/mL (100-mcg dose) were reached 0.4 hours after dosing. Using a specific radioimmunoassay, intravenous and subcutaneous doses were found to be bioequivalent. Peak concentrations and area under the curve (AUC) values were dose proportional both after subcutaneous or intravenous single doses up to 400 mcg and with multiple doses of 200 mcg 3 times daily (600 mcg/day). Clearance was reduced by about 66% suggesting nonlinear kinetics of the drug at daily doses of 600 mcg/day compared to 150 mcg/day. The relative decrease in clearance with doses above 600 mcg/day is not defined.

In healthy volunteers, the distribution of octreotide from plasma was rapid (tα1/2 = 0.2 h), the volume of distribution (Vdss) was estimated to be 13.6 L and the total body clearance was 10 L/h.

In blood, the distribution of octreotide into the erythrocytes was found to be negligible and about 65% was bound in the plasma in a concentration-independent manner. Binding was mainly to lipoprotein and, to a lesser extent, to albumin.

The elimination of octreotide from plasma had an apparent half-life of 1.7 hours, compared with the 1-3 minutes with the natural hormone, somatostatin. The duration of action of subcutaneously administered Sandostatin Injection solution is variable but extends up to 12 hours depending upon the type of tumor, necessitating multiple daily dosing with this immediate-release dosage form. About 32% of the dose is excreted unchanged into the urine. In an elderly population, dose adjustments may be necessary due to a significant increase in the half-life (46%) and a significant decrease in the clearance (26%) of the drug.

In patients with acromegaly, the pharmacokinetics differ somewhat from those in healthy volunteers. A mean peak concentration of 2.8 ng/mL (100-mcg dose) was reached in 0.7 hours after subcutaneous dosing. The Vdss was estimated to be 21.6 ± 8.5 L and the total body clearance was increased to 18 L/h. The mean percent of the drug bound was 41.2%. The disposition and elimination half-lives were similar to normals.

The half-life in renal-impaired patients was slightly longer than normal subjects (2.4-3.1 h versus 1.9 h). The clearance in renal-impaired patients was 7.3-8.8 L/h as compared to 8.3 L/h in healthy subjects. In patients with severe renal failure requiring dialysis, clearance was reduced to about half that found in healthy subjects (from approximately 10 L/h to 4.5 L/h).

Patients with liver cirrhosis showed prolonged elimination of drug, with octreotide half-life increasing to 3.7 h and total body clearance decreasing to 5.9 L/h, whereas patients with fatty liver disease showed half-life increasing to 3.4 h and total body clearance of 8.4 L/h. In normal subjects, octreotide half-life is 1.9 h and the clearance is 8.3 L/h which is comparable with the clearance in fatty-liver patients.

SANDOSTATIN LAR DEPOT

The magnitude and duration of octreotide serum concentrations after an intramuscular injection of the long-acting depot formulation SANDOSTATIN LAR DEPOT reflect the release of drug from the microsphere polymer matrix. Drug release is governed by the slow biodegradation of the microspheres in the muscle, but once present in the systemic circulation, octreotide distributes and is eliminated according to its known pharmacokinetic properties which are as follows.

After a single IM injection of the long-acting depot dosage form SANDOSTATIN LAR DEPOT in healthy volunteer subjects, the serum octreotide concentration reached a transient initial peak of about 0.03 ng/mL/mg within 1 hour after administration progressively declining over the following 3 to 5 days to a nadir of < 0.01 ng/mL/mg, then slowly increasing and reaching a plateau about 2 to 3 weeks postinjection. Plateau concentrations were maintained over a period of nearly 2 to 3 weeks, showing dose proportional peak concentrations of about 0.07 ng/mL/mg. After about 6 weeks postinjection, octreotide concentration slowly decreased, to < 0.01 ng/mL/mg by Weeks 12 to 13, concomitant with the terminal degradation phase of the polymer matrix of the dosage form. The relative bioavailability of the long-acting release SANDOSTATIN LAR DEPOT compared to immediate-release Sandostatin Injection solution given subcutaneously was 60% to 63%.

In patients with acromegaly, the octreotide concentrations after single doses of 10 mg, 20 mg, and 30 mg SANDOSTATIN LAR DEPOT were dose proportional. The transient Day 1 peak, amounting to 0.3 ng/mL, 0.8 ng/mL, and 1.3 ng/mL, respectively, was followed by plateau concentrations of 0.5 ng/mL, 1.3 ng/mL, and 2.0 ng/mL, respectively, achieved about 3 weeks postinjection. These plateau concentrations were maintained for nearly 2 weeks.

Following multiple doses of SANDOSTATIN LAR DEPOT given every 4 weeks, steady-state octreotide serum concentrations were achieved after the third injection. Concentrations were dose proportional and higher by a factor of approximately 1.6 to 2.0 compared to the concentrations after a single dose. The steady-state octreotide concentrations were 1.2 ng/mL and 2.1 ng/mL, respectively, at trough and 1.6 ng/mL and 2.6 ng/mL, respectively, at peak with 20 mg and 30 mg SANDOSTATIN LAR DEPOT given every 4 weeks. No accumulation of octreotide beyond that expected from the overlapping release profiles occurred over a duration of up to 28 monthly injections of SANDOSTATIN LAR DEPOT. With the long-acting depot formulation SANDOSTATIN LAR DEPOT administered IM every 4 weeks the peak-to-trough variation in octreotide concentrations ranged from 44% to 68%, compared to the 163% to 209% variation encountered with the daily subcutaneous three times daily regimen of Sandostatin Injection solution.

In patients with carcinoid tumors, the mean octreotide concentrations after 6 doses of 10 mg, 20 mg, and 30 mg SANDOSTATIN LAR DEPOT administered by IM injection every 4 weeks were 1.2 ng/mL, 2.5 ng/mL, and 4.2 ng/mL, respectively. Concentrations were dose proportional and steady-state concentrations were reached after 2 injections of 20 mg and 30 mg and after 3 injections of 10 mg.

SANDOSTATIN LAR DEPOT has not been studied in patients with renal impairment.

SANDOSTATIN LAR DEPOT has not been studied in patients with hepatic impairment.

13 NONCLINICAL TOXICOLOGY

13.1 Carcinogenesis, Mutagenesis, Impairment of Fertility

Studies in laboratory animals have demonstrated no mutagenic potential of Sandostatin. No mutagenic potential of the polymeric carrier in SANDOSTATIN LAR DEPOT, D,L-lactic and glycolic acids copolymer, was observed in the Ames mutagenicity test.

No carcinogenic potential was demonstrated in mice treated subcutaneously with octreotide for 85-99 weeks at doses up to 2 mg/kg/day (8-times the human exposure based on BSA). In a 116-week subcutaneous study in rats administered octreotide, a 27% and 12% incidence of injection-site sarcomas or squamous cell carcinomas was observed in males and females, respectively, at the highest dose level of 1.25 mg/kg/day (10-times the human exposure based on BSA) compared to an incidence of 8% to 10% in the vehicle-control groups. The increased incidence of injection-site tumors was most probably caused by irritation and the high sensitivity of the rat to repeated subcutaneous injections at the same site. Rotating injection sites would prevent chronic irritation in humans. There have been no reports of injection-site tumors in patients treated with Sandostatin Injection for at least 5 years. There was also a 15% incidence of uterine adenocarcinomas in the 1.25 mg/kg/day females compared to 7% in the saline-control females and 0% in the vehicle-control females. The presence of endometritis coupled with the absence of corpora lutea, the reduction in mammary fibroadenomas, and the presence of uterine dilatation suggest that the uterine tumors were associated with estrogen dominance in the aged female rats which does not occur in humans.

Octreotide did not impair fertility in rats at doses up to 1 mg/kg/day, which represents 7-times the human exposure based on BSA.

14 CLINICAL STUDIES

14.1 Acromegaly

The clinical trials of SANDOSTATIN LAR DEPOT were performed in patients who had been receiving Sandostatin Injection for a period of weeks to as long as 10 years. The acromegaly studies with SANDOSTATIN LAR DEPOT described below were performed in patients who achieved GH levels of < 10 ng/mL (and, in most cases < 5 ng/mL) while on subcutaneous Sandostatin Injection. However, some patients enrolled were partial responders to subcutaneous Sandostatin Injection, i.e., GH levels were reduced by > 50% on subcutaneous Sandostatin Injection compared to the untreated state, although not suppressed to < 5 ng/mL.

SANDOSTATIN LAR DEPOT was evaluated in three clinical trials in acromegalic patients.

In 2 of the clinical trials, a total of 101 patients were entered who had, in most cases, achieved a GH level < 5 ng/mL on Sandostatin Injection given in doses of 100 mcg or 200 mcg three times daily. Most patients were switched to 20 mg or 30 mg doses of SANDOSTATIN LAR DEPOT given once every 4 weeks for up to 27 to 28 injections. A few patients received doses of 10 mg and a few required doses of 40 mg. Growth hormone and IGF-1 levels were at least as well controlled with SANDOSTATIN LAR DEPOT as they had been on Sandostatin Injection and this level of control remained for the entire duration of the trials.

A third trial was a 12-month study that enrolled 151 patients who had a GH level < 10 ng/mL after treatment with Sandostatin Injection (most had levels < 5 ng/mL). The starting dose of SANDOSTATIN LAR DEPOT was 20 mg every 4 weeks for 3 doses. Thereafter, patients received 10 mg, 20 mg, or 30 mg every 4 weeks, depending upon the degree of GH suppression [see Dosage and Administration (2)]. Growth hormone and IGF-1 were at least as well controlled on SANDOSTATIN LAR DEPOT as they had been on Sandostatin Injection.

Table 5 summarizes the data on hormonal control (GH and IGF-1) for those patients in the first two clinical trials who received all 27 to 28 injections of SANDOSTATIN LAR DEPOT.

Table 5. Hormonal Response in Acromegalic Patients Receiving 27 to 28 Injections During^1 Treatment With SANDOSTATIN LAR DEPOT
Mean Hormone Level | Sandostatin Injection S.C. |  | SANDOSTATIN LAR DEPOT
 | n | % | n | %
GH < 5.0 ng/mL | 69/88 | 78 | 73/88 | 83
< 2.5 ng/mL | 44/88 | 50 | 41/88 | 47
< 1.0 ng/mL | 6/88 | 7 | 10/88 | 11
IGF-1 normalized | 36/88 | 41 | 45/88 | 51
GH < 5.0 ng/mL + IGF-1 normalized | 36/88 | 41 | 45/88 | 51
< 2.5 ng/mL + IGF-1 normalized | 30/88 | 34 | 37/88 | 42
< 1.0 ng/mL + IGF-1 normalized | 5/88 | 6 | 10/88 | 11
^1Average of monthly levels of GH and IGF-1 over the course of the trials.

For the 88 patients in Table 5, a mean GH level of < 2.5 ng/mL was observed in 47% receiving SANDOSTATIN LAR DEPOT. Over the course of the trials, 42% of patients maintained mean growth hormone levels of < 2.5 ng/mL and mean normal IGF-1 levels.

Table 6 summarizes the data on hormonal control (GH and IGF-1) for those patients in the third clinical trial who received all 12 injections of SANDOSTATIN LAR DEPOT.

Table 6. Hormonal Response in Acromegalic Patients Receiving 12 Injections During^1 Treatment With SANDOSTATIN LAR DEPOT
Mean Hormone Level | Sandostatin Injection S.C. |  | SANDOSTATIN LAR DEPOT
 | n | % | n | %
GH < 5.0 ng/mL | 116/122 | 95 | 118/122 | 97
< 2.5 ng/mL | 84/122 | 69 | 80/122 | 66
< 1.0 ng/mL | 25/122 | 21 | 28/122 | 23
IGF-1 normalized | 82/122 | 67 | 82/122 | 67
GH < 5.0 ng/mL + IGF-1 normalized | 80/122 | 66 | 82/122 | 67
< 2.5 ng/mL + IGF-1 normalized | 65/122 | 53 | 70/122 | 57
< 1.0 ng/mL + IGF-1 normalized | 23/122 | 19 | 27/122 | 22
^1Average of monthly levels of GH and IGF-1 over the course of the trial.

For the 122 patients in Table 6, who received all 12 injections in the third trial, a mean GH level of < 2.5 ng/mL was observed in 66% receiving SANDOSTATIN LAR DEPOT. Over the course of the trial, 57% of patients maintained mean growth hormone levels of < 2.5 ng/mL and mean normal IGF-1 levels. In comparing the hormonal response in these trials, note that a higher percentage of patients in the third trial suppressed their mean GH to < 5 ng/mL on subcutaneous Sandostatin Injection, 95%, compared to 78% across the 2 previous trials.

In all 3 trials, GH, IGF-1, and clinical symptoms were similarly controlled on SANDOSTATIN LAR DEPOT as they had been on Sandostatin Injection.

Of the 25 patients who completed the trials and were partial responders to Sandostatin Injection (GH > 5.0 ng/mL but reduced by > 50% relative to untreated levels), 1 patient (4%) responded to SANDOSTATIN LAR DEPOT with a reduction of GH to < 2.5 ng/mL and 8 patients (32%) responded with a reduction of GH to < 5.0 ng/mL.

Two open-label clinical studies investigated a 48-week treatment with SANDOSTATIN LAR DEPOT in 143 untreated (de novo) acromegalic patients. The median reduction in tumor volume was 20.6% in Study 1 (49 patients) at 24 weeks and 24.5% in Study 2 (94 patients) at 24 weeks and 36.2% at 48 weeks.

14.2 Carcinoid Syndrome

A 6-month clinical trial of malignant carcinoid syndrome was performed in 93 patients who had previously been shown to be responsive to Sandostatin Injection. Sixty-seven (67) patients were randomized at baseline to receive double-blind doses of 10 mg, 20 mg, or 30 mg SANDOSTATIN LAR DEPOT every 28 days and 26 patients continued, unblinded, on their previous Sandostatin Injection regimen (100 to 300 mcg three times daily).

In any given month after steady-state levels of octreotide were reached, approximately 35% to 40% of the patients who received SANDOSTATIN LAR DEPOT required supplemental subcutaneous Sandostatin Injection therapy usually for a few days, to control exacerbation of carcinoid symptoms. In any given month, the percentage of patients randomized to subcutaneous Sandostatin Injection, who required supplemental treatment with an increased dose of Sandostatin Injection, was similar to the percentage of patients randomized to SANDOSTATIN LAR DEPOT. Over the 6-month treatment period, approximately 50% to 70% of patients who completed the trial on SANDOSTATIN LAR DEPOT required subcutaneous Sandostatin Injection supplemental therapy to control exacerbation of carcinoid symptoms although steady-state serum SANDOSTATIN LAR DEPOT levels had been reached.

Table 7 presents the average number of daily stools and flushing episodes in malignant carcinoid patients.

Table 7. Average Number of Daily Stools and Flushing Episodes in Patients With Malignant Carcinoid Syndrome
Treatment |  | Daily Stools (Average Number) |  | Daily Flushing Episodes (Average Number)
 | n | Baseline | Last Visit | Baseline | Last Visit
Sandostatin Injection S.C. | 26 | 3.7 | 2.6 | 3.0 | 0.5
SANDOSTATIN LAR DEPOT
10 mg | 22 | 4.6 | 2.8 | 3.0 | 0.9
20 mg | 20 | 4.0 | 2.1 | 5.9 | 0.6
30 mg | 24 | 4.9 | 2.8 | 6.1 | 1.0

Overall, mean daily stool frequency was as well controlled on SANDOSTATIN LAR DEPOT as on Sandostatin Injection (approximately 2 to 2.5 stools/day).

Mean daily flushing episodes were similar at all doses of SANDOSTATIN LAR DEPOT and on Sandostatin Injection (approximately 0.5 to 1 episode/day).

In a subset of patients with variable severity of disease, median 24 hour urinary 5-HIAA (5-hydroxyindole acetic acid) levels were reduced by 38% to 50% in the groups randomized to SANDOSTATIN LAR DEPOT.

The reductions are within the range reported in the published literature for patients treated with octreotide (about 10% to 50%).

Seventy-eight (78) patients with malignant carcinoid syndrome who had participated in this 6-month trial subsequently participated in a 12-month extension study in which they received 12 injections of SANDOSTATIN LAR DEPOT at 4-week intervals. For those who remained in the extension trial, diarrhea and flushing were as well controlled as during the 6-month trial. Because malignant carcinoid disease is progressive, as expected, a number of deaths (8 patients: 10%) occurred due to disease progression or complications from the underlying disease. An additional 22% of patients prematurely discontinued SANDOSTATIN LAR DEPOT due to disease progression or worsening of carcinoid symptoms.

16 HOW SUPPLIED/STORAGE AND HANDLING

SANDOSTATIN LAR DEPOT is available in single-dose kits containing a 6-mL single-dose vial of 10 mg, 20 mg or 30 mg strength, a prefilled syringe containing 2 mL of diluent, one vial adapter, and one sterile 1½” 19 gauge safety injection needle. An instruction booklet for the preparation of drug suspension for injection is also included with each kit.

Drug Product Kits

10 mg kit NDC 0078-0811-81

20 mg kit NDC 0078-0818-81

30 mg kit NDC 0078-0825-81

Demonstration kit 0078-9825-81

For prolonged storage, SANDOSTATIN LAR DEPOT should be stored at refrigerated temperatures between 2°C to 8°C (36°F to 46°F) and protected from light until the time of use. SANDOSTATIN LAR DEPOT drug product kit should remain at room temperature for 30 to 60 minutes prior to preparation of the drug suspension. However, after preparation the drug suspension must be administered immediately.

17 PATIENT COUNSELING INFORMATION

Cholelithiasis and Complications of Cholelithiasis

Advise patients to contact their healthcare provider if they experience signs or symptoms of gallstones (cholelithiasis) or complications of cholelithiasis (e.g., cholecystitis, cholangitis and pancreatitis) [see Warnings and Precautions (5.1)].

Carcinoid Tumors and VIPomas

Patients with carcinoid tumors and VIPomas should be advised to adhere closely to their scheduled return visits for reinjection in order to minimize exacerbation of symptoms [see Dosage and Administration (2.2)].

Acromegaly

Patients with acromegaly should also be urged to adhere to their return visit schedule to help assure steady control of GH and IGF-1 levels [see Dosage and Administration (2.1)].

Steatorrhea and Malabsorption of Dietary Fats

Advise patients to contact their healthcare provider if they experience new or worsening symptoms of steatorrhea, stool discoloration, loose stools, abdominal bloating, and weight loss [see Warnings and Precautions (5.5)].

Pregnancy

Inform female patients that treatment with SANDOSTATIN LAR DEPOT may result in unintended pregnancy [see Use in Specific Populations (8.3)].

Distributed by:
Novartis Pharmaceuticals Corporation
East Hanover, New Jersey 07936

© Novartis

T2024-51

PRINCIPAL DISPLAY PANEL

NDC 0078-0811-81

Sandostatin® LAR Depot

(octreotide acetate) for injectable suspension,
for gluteal intramuscular use

10 mg

For Intragluteal Injection

Rx only

NOVARTIS

PRINCIPAL DISPLAY PANEL

NDC 0078-0818-81

Sandostatin® LAR Depot

(octreotide acetate) for injectable suspension,
for gluteal intramuscular use

20 mg

For Intragluteal Injection

Rx only

NOVARTIS

PRINCIPAL DISPLAY PANEL

NDC 0078-0825-81

Sandostatin® LAR Depot

(octreotide acetate) for injectable suspension,
for gluteal intramuscular use

30 mg

For Intragluteal Injection

Rx only

NOVARTIS